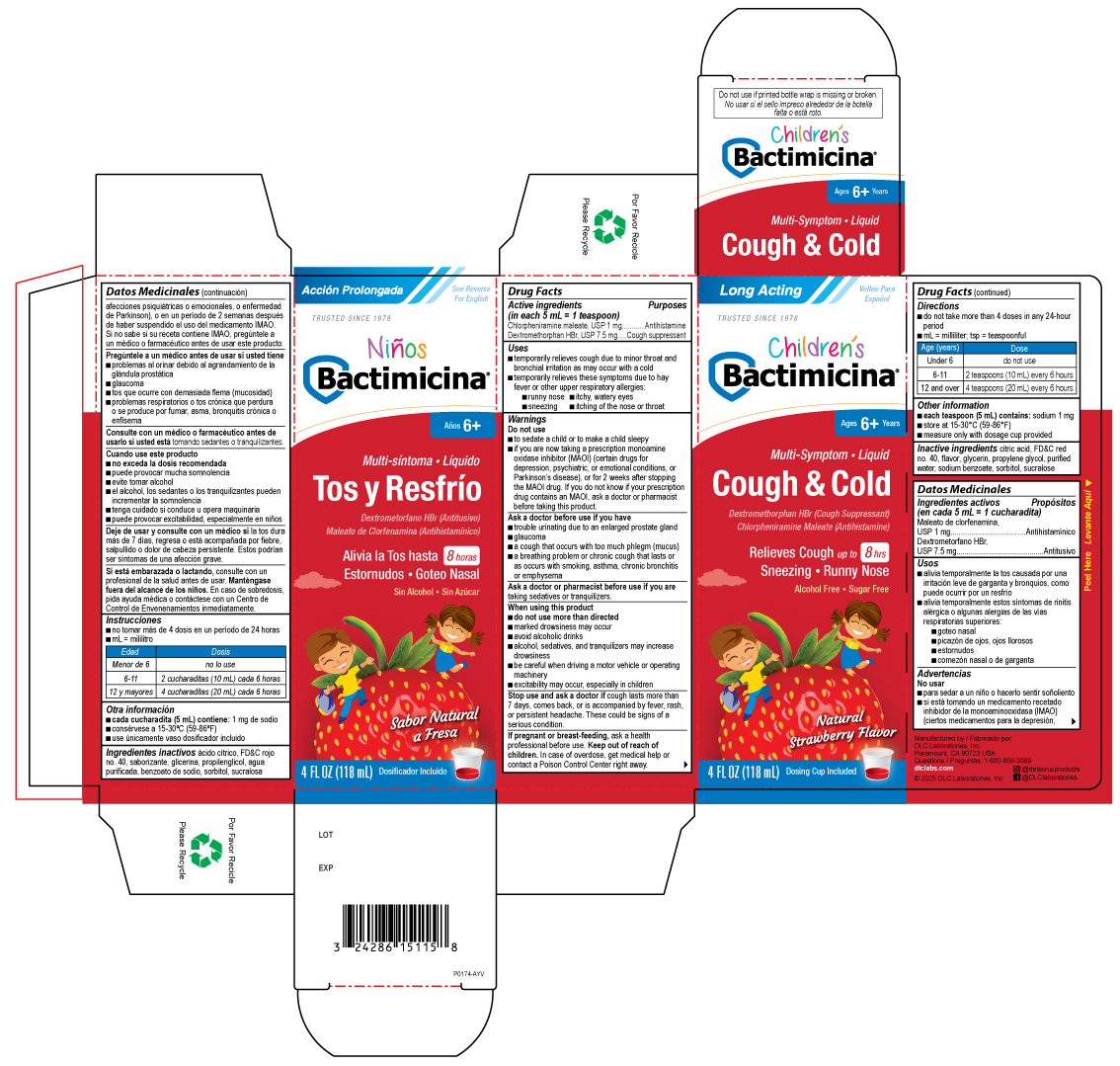 DRUG LABEL: Bactimicina Childrens Cough and Cold
NDC: 24286-1551 | Form: LIQUID
Manufacturer: DLC Laboratories, Inc.
Category: otc | Type: HUMAN OTC DRUG LABEL
Date: 20250515

ACTIVE INGREDIENTS: CHLORPHENIRAMINE MALEATE 1 mg/5 mL; DEXTROMETHORPHAN HYDROBROMIDE 7.5 mg/5 mL
INACTIVE INGREDIENTS: CITRIC ACID MONOHYDRATE; FD&C RED NO. 40; PROPYLENE GLYCOL; WATER; SODIUM BENZOATE; SORBITOL; SUCRALOSE; GLYCERIN

Bactimicina Liquid Children's Cough and Cold

Drug Facts

ACTIVE INGREDIENT

PURPOSE

Active ingredients (in each 5 mL = 1 teaspoon) | Purposes
Chlorpheniramine maleate, USP 1 mg | Antihistamine
Dextromethorphan HBr, USP 7.5 mg | Cough suppressant

Uses

- temporarily relieves cough due to minor throat and bronchial irritation as may occur with a cold
- temporarily relieves these symptoms due to hay fever or other upper respiratory allergies:
  - runny nose
  - itchy, watery eyes
  - sneezing
  - itching of the nose or throat

Warnings

Do not use

- to sedate a child or to make a child sleepy
- if you are now taking a prescription monoamine oxidase inhibitor (MAOI) (certain drugs for depression, psychiatric, or emotional conditions, or Parkinson's disease), or for 2 weeks after stopping the MAOI drug. If you do not know if your prescription drug contains an MAOI, ask a doctor or pharmacist before taking this product.

Ask a doctor before use if you have

- trouble urinating due to an enlarged prostate gland
- glaucoma
- a cough that occurs with too much phlegm (mucus)
- a breathing problem or chronic cough that lasts or as occurs with smoking, asthma, chronic bronchitis or emphysema

Ask a doctor or pharmacist before use if you are taking sedatives or tranquilizers.

When using this product

- do not use more than directed
- marked drowsiness may occur
- avoid alcoholic drinks
- alcohol, sedatives, and tranquilizers may increase drowsiness
- be careful when driving a motor vehicle or operating machinery
- excitability may occur, especially in children

Stop use and ask a doctor if cough lasts more than 7 days, comes back, or is accompanied by fever, rash, or persistent headache. These could be signs of a serious condition.

PREGNANCY OR BREAST FEEDING

If pregnant or breast-feeding, ask a health professional before use.

Keep out of reach of children. In case of overdose, get medical help or contact a Poison Control Center right away.

Directions

- do not take more than 4 doses in any 24-hour period
- mL=mililiter; tsp=teaspoonful

Age (years) | Dose
Under 6 | do not use
6-11 | 2 teaspoons (10 mL) every 6 hours
12 and over | 4 teaspoons (20 mL) every 6 hours

RECENT MAJOR CHANGES

ml=mililiter; tsp=teaspoonful

Other information

- each teaspoon (5 mL) contains: sodium 1 mg
- store at 15-30°C (59-86°F)
- measure only with dosage cup provided
- do not use if printed bottle wrap is missing or broken.

Inactive ingredients

citric acid, FD&C red no. 40, flavor, glycerin, propylene glycol, purified water, sodium benzoate, sorbitol, sucralose

Questions

1-800-858-3889

Manufactured by:
DLC Laboratories, Inc.
Paramount, CA 90723 USA

PRINCIPAL DISPLAY PANEL - 118 mL Bottle Label

Long Acting

Voltee Para

Espanol

TRUSTED SINCE 1978

Children's

Bactimicina®

Ages 6+ Years

Milti-Symptom • Liquid

Cough & Cold

Dextromethorphan HBr (Cough Suppressant)

Chlorpheniramine Maleate (Antihistamine)

Relieves Cough up to 8hrs

Sneezing • Runny Nose

Alcohol Free• Sugar Free

Natural Strawberry Flavor

4 FL OZ (118 mL) Dosing Cup Included